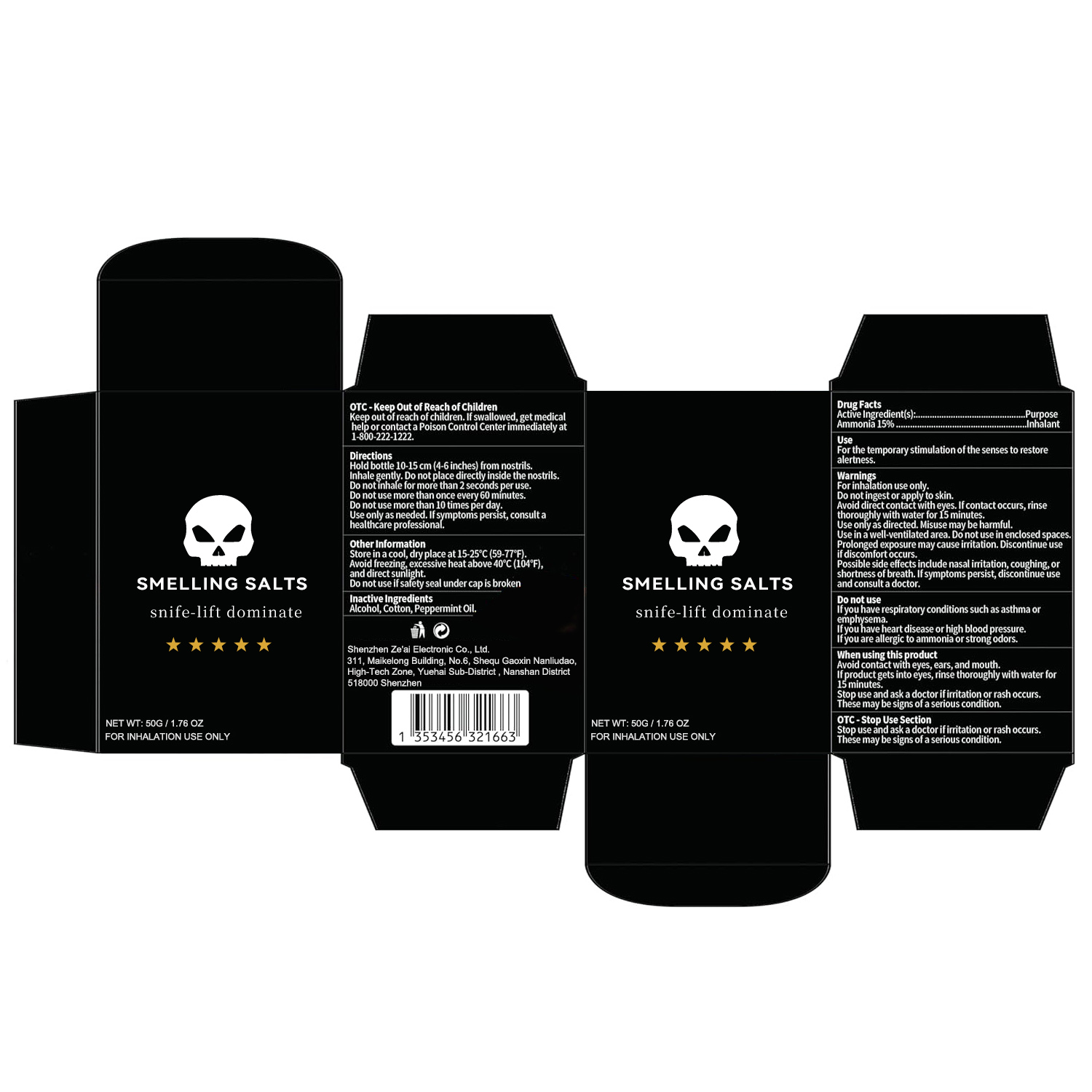 DRUG LABEL: smelling salts
NDC: 85765-001 | Form: POWDER
Manufacturer: Shenzhen Ze'ai Electronic Co., Ltd.
Category: otc | Type: HUMAN OTC DRUG LABEL
Date: 20250605

ACTIVE INGREDIENTS: AMMONIA 15 g/100 g
INACTIVE INGREDIENTS: AROMATIC-L-AMINO-ACID DECARBOXYLASE; SOLVENT BLUE 102; ALCOHOL; COTTON; PEPPERMINT OIL

85765-001 smelling salts

ACTIVE INGREDIENT

Ammonia 15%

PURPOSE

Inhalant

INDICATIONS AND USAGE

For the temporary stimulation of the senses to restore alertness.

WARNINGS

For inhalation use only.
Do not ingest or apply to skin.
Avoid direct contact with eyes. lfcontact occurs, rinsethoroughly with water for 15 minutes.
Use only as directed. Misuse may be harmful
Use in a well-ventilated area, Do not use in enclosed spaces Prolonged exposure may cause irritation. Discontinue useif discomfort occurs.
Possible side effects include nasal imitation, coughing, orshortness ofbreath. lfsymptoms persist, discontinue useand consult a doctor.

DO NOT USE

lf you have respiratory conditions such as asthma oremphysema.
lf you have heart disease or high blood pressure.
If you are allergic to ammonia orstrong odors.

WHEN USING

Avoid contact with eyes, ears, and mouth.
lf product gets into eyes, rinse thoroughly with water for 15 minutes.
Stop use and ask a doctor if irritation or rash occurs.
These may be signs of a serious condition.

Stop use and ask a doctor ifirritation or rash occurs.
These may be signs of a serious condition.

Keep out ofreach ofchildren.lfswallowed, get medical
help or contact a Poison Control Center immediately at
1-800-222-1222

DOSAGE AND ADMINISTRATION

Hold bottle 10-15 cm (4-6 inches) from nostrils.
Inhale gently. Do not place directly inside the nostrils.
Do notinhale for more than 2 seconds per use.
Do not use more than once every 60 minutes.
Do not use more than 10 times per day.
Use only as needed, lfsymptoms persist, consult ahealthcare professional!

INACTIVE INGREDIENT

aromatic
solvent
Alcohol
Cotton
Peppermint Oil